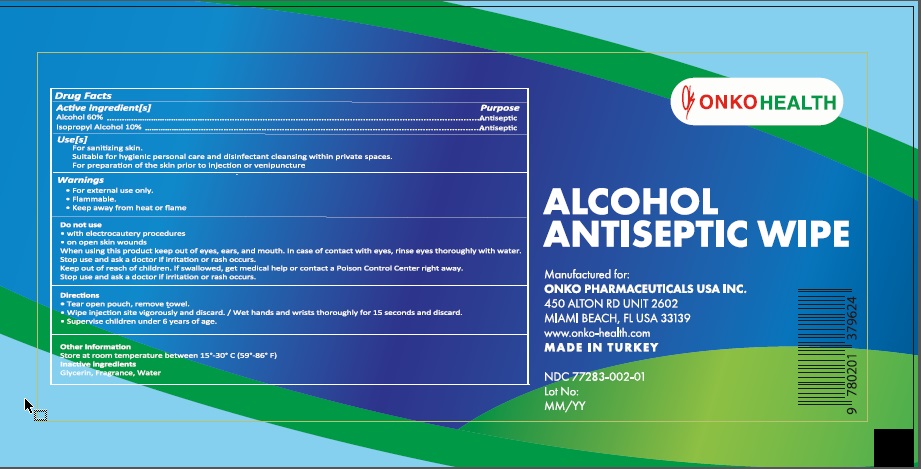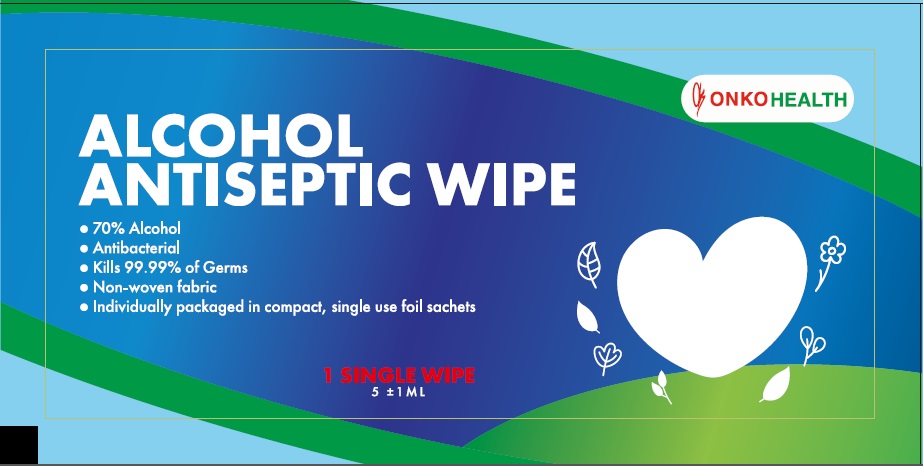 DRUG LABEL: ONKO HEALTH ALCOHOL ANTISEPTIC WIPE
NDC: 77283-002 | Form: CLOTH
Manufacturer: ONKO PHARMACEUTICALS USA INC.
Category: otc | Type: HUMAN OTC DRUG LABEL
Date: 20201120

ACTIVE INGREDIENTS: ALCOHOL 60 mL/100 mL; ISOPROPYL ALCOHOL 10 mL/100 mL
INACTIVE INGREDIENTS: GLYCERIN; WATER

Active Ingredients

Alcohol 60% v/v.

Isopropyl alcohol 10 % v/v.

Purpose

Antiseptic

Use

- For sanitizing skin.
- Suitable for hygienic personal care and disinfectant cleansing within private spaces.
- For preparation of the skin prior to injection or venipuncture.

Warnings

For external use only.

Flammable. Keep away from heat or flame.

Do not use

- with electrocautery procedures
- on open skin wounds

When using this product keep out of eyes, ears, and mouth. In case of contact with eyes, rinse eyes thoroughly with water.

Stop use and ask a doctor if irritation or rash occurs.

Keep out of reach of children. If swallowed, get medical help or contact a Poison Control Center right away.

Directions

For single pack;

• Tear open pouch, remove towel.

• Wipe injection site vigorously and discard. / Wet hands and wrists thoroughly for 15 seconds and discard.

• Supervise children under 6 years of age.

For multi pack;

• Open clip-lid.

• Remove moist towels to clean skin as required.

• Wipe injection site vigorously and discard. / Wet hands and wrists thoroughly for 15 seconds and discard.

• Close lid when not in use to keep remaining towels moist.

• Supervise children under 6 years of age.

Other information

- Store between 15-30oC (59-86oF)
- Avoid freezing and excessive heat above 40oC (104oF)

Inactive ingredients

Glycerin, Fragrance, Water.